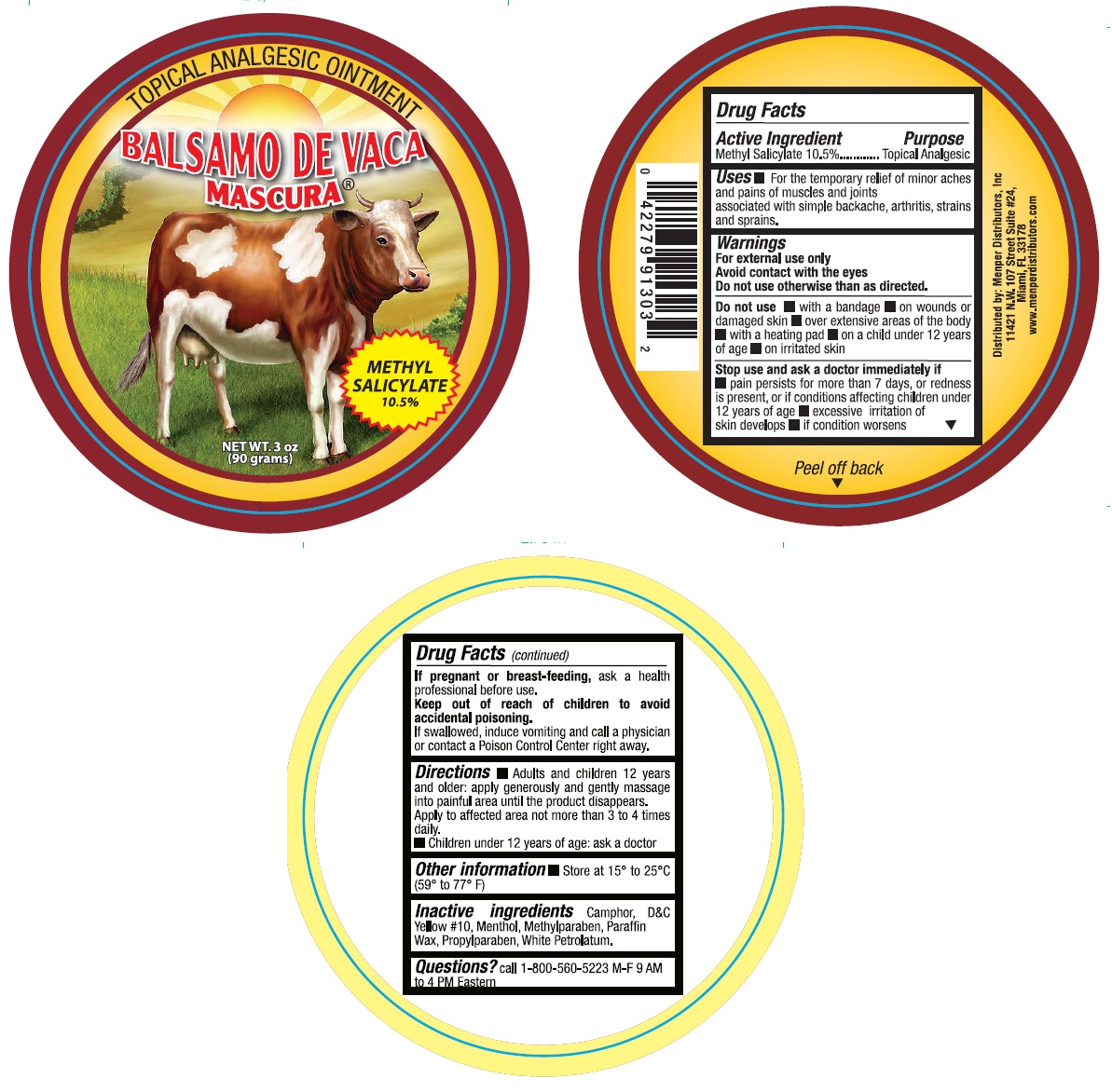 DRUG LABEL: Balsamo de Vaca Mascura
NDC: 53145-403 | Form: OINTMENT
Manufacturer: Menper Distributors Inc.
Category: otc | Type: HUMAN OTC DRUG LABEL
Date: 20250722

ACTIVE INGREDIENTS: METHYL SALICYLATE 10.5 g/100 g
INACTIVE INGREDIENTS: CAMPHOR (SYNTHETIC); D&C YELLOW NO. 10; MENTHOL; METHYLPARABEN; PARAFFIN; PETROLATUM; PROPYLPARABEN

Balsamo de Vaca Mascura

Active Ingredient Purpose
Methyl Salicylate 10.5 % ............................................External Analgesic

Purpose

External Analgesic

Uses

For the temporary relief of minor aches and pains of muscles and joints associated with simple backache, arthritis, strains and sprains

Warnings

For external use only

Do not use

- on wounds or damage skin
- with a heating pad
- on a child under 12 years of age
- over extensive areas of the body
- on irritated skin
- woth a bandage

Ask doctor before use if you have

redness over the affected area

When using this product

- avoid contact with eyes or mucous membranes
- do not bandage

Stop use and ask a doctor if

- condition worsens or symptoms persist for more than 7 days
- symptoms clear up and occur again within a few days
- excessive skin irritation occurs

if pregnant or breast-feeding

ask a health professional before use

keep out of reach of children to avoid accidental poisoning.

If swallowed, induce vomiting and call a physician or contact a Poison Control Center right away.

Directions

- Use only as directed
- adults and children 12 years and older apply to affected area not more tha 3 to 4 times daily
- children under 12 years of age: ask a doctor

Other information

- store at 15° to 25° C (59° to 77° F)

Inactive Ingredients:

Camphor, D&C yellow 10#, menthol, methylparaben, paraffin wax, propylparaben, white petrolatum.

Questions?

call 1-800-60-5223 M-F 9 AM to 4 PM Eastern